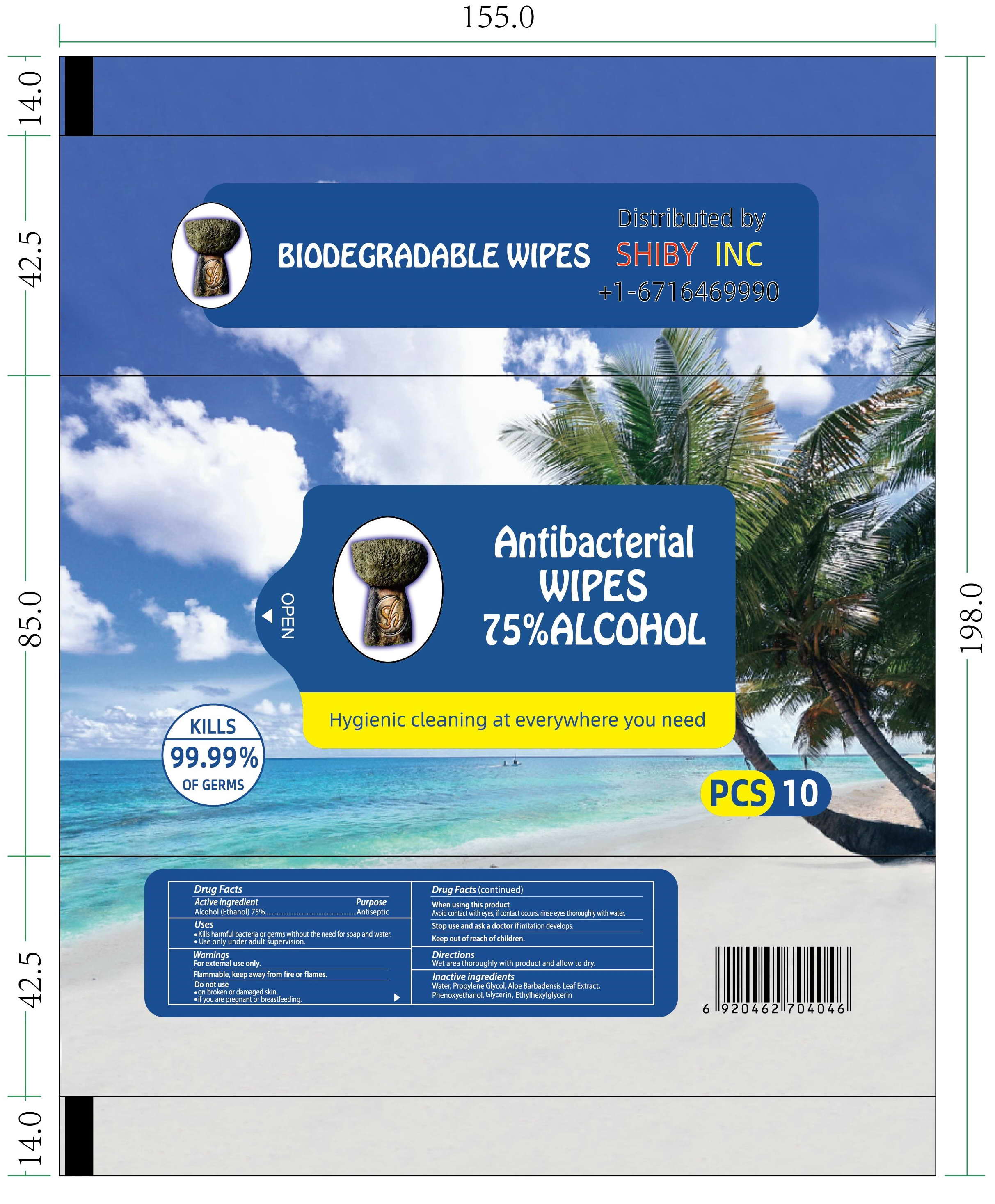 DRUG LABEL: Alcohol Wipes
NDC: 77119-102 | Form: CLOTH
Manufacturer: Guangzhou Shentai Hygienic Products Co., Ltd.
Category: otc | Type: HUMAN OTC DRUG LABEL
Date: 20210708

ACTIVE INGREDIENTS: CETYLPYRIDINIUM CHLORIDE 0.025 g/100 g; ALCOHOL 75 g/100 g; BENZALKONIUM CHLORIDE 0.0125 g/100 g
INACTIVE INGREDIENTS: ALOE EMODIN 0.1 g/100 g; ETHYLHEXYLGLYCERIN 0.005 g/100 g; GLYCERIN 0.0125 g/100 g; WATER 24.695 g/100 g; PROPYLENE GLYCOL 0.125 g/100 g; PHENOXYETHANOL 0.025 g/100 g

75% Alcohol Wipes Biodegradable

Biodegradable Wipes. Alcohol Wipes. 75% Alcohol

Active Ingredient(s)

Alcohol: 75%;

Purpose

Antiseptic, Kill 99.99% of Germs

Uses

-- Kills harmful bacteria or germs without the need for soap and water.
-- Use only under adult supervision

Warnings

-- For external use only .
-- Flammable, keep away from fire or flames .

Do not use

-- on broken or damaged skin .
-- if you are pregnant or breastfeeding

When using this product

Avoid contact with eyes, if contact occurs, rinse eyes thoroughly with water.

Stop use and ask doctor if irritation develops.
Keep out of reach of children.

Keep out of reach of children. If swallowed, get medical help or contact a Poison Control Center right away.

Directions

Wet area thoroughly with product and allow to dry.

Other information

- Store between 15-30C (59-86F)
- Avoid freezing and excessive heat above 40C (104F)

Inactive ingredients

Water, Propylene Glycol, Aloe Barbadensis Leaf Extract, Phenoxyethanol, Glycerin, Ethylhexylglycerin

Package Label - Principal Display Panel

NDC: 77119-102-01;

10 pcs in 1 BAG;

1 BAG Approximately 62g.